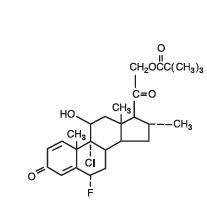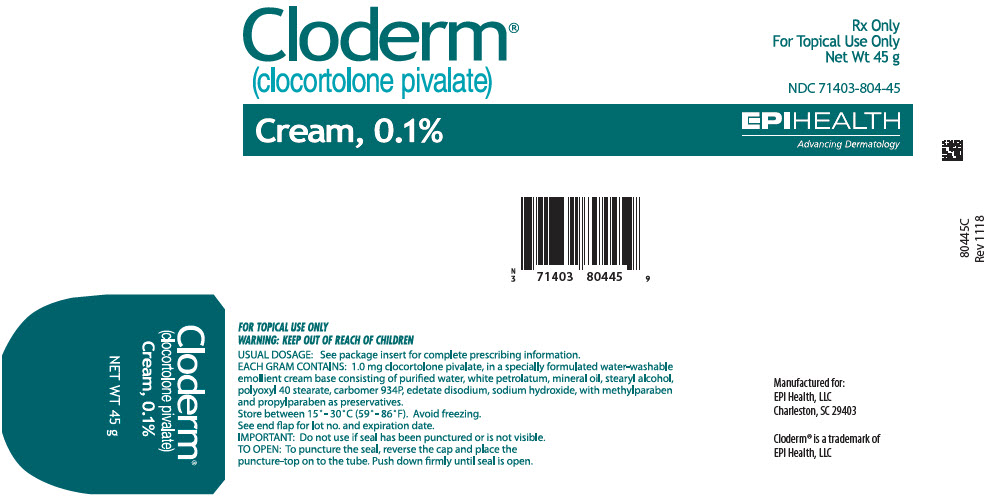 DRUG LABEL: Cloderm
NDC: 71403-804 | Form: CREAM
Manufacturer: EPI Health, Inc
Category: prescription | Type: HUMAN PRESCRIPTION DRUG LABEL
Date: 20221102

ACTIVE INGREDIENTS: clocortolone pivalate 1 mg/1 g
INACTIVE INGREDIENTS: Water; PETROLATUM; Mineral Oil; STEARYL ALCOHOL; POLYOXYL 40 STEARATE; CARBOMER HOMOPOLYMER TYPE B (ALLYL PENTAERYTHRITOL CROSSLINKED); EDETATE DISODIUM; Sodium Hydroxide; METHYLPARABEN; PROPYLPARABEN

Cloderm® Cream, 0.1%
(clocortolone pivalate)

Rx Only

FOR TOPICAL DERMATOLOGIC USE ONLY–
NOT FOR OPHTHALMIC, ORAL, OR INTRAVAGINAL USE.
WARNING: KEEP OUT OF REACH OF CHILDREN

DESCRIPTION

Cloderm Cream 0.1% contains the medium potency topical corticosteroid, clocortolone pivalate, in a specially formulated water-washable emollient cream base consisting of purified water, white petrolatum, mineral oil, stearyl alcohol, polyoxyl 40 stearate, carbomer 934P, edetate disodium, sodium hydroxide, with methylparaben and propylparaben as preservatives.

Chemically, clocortolone pivalate is 9-chloro-6α-fluoro-11β, 21-dihydroxy-16α methylpregna-1, 4-diene-3, 20-dione 21-pivalate. Its structure is as follows:

CLINICAL PHARMACOLOGY

Topical corticosteroids share anti-inflammatory, antipruritic and vasoconstrictive actions.

The mechanism of anti-inflammatory activity of the topical corticosteroids is unclear. Various laboratory methods, including vasoconstrictor assays, are used to compare and predict potencies and/or clinical efficacies of the topical corticosteroids. There is some evidence to suggest that a recognizable correlation exists between vasoconstrictor potency and therapeutic efficacy in man.

Pharmacokinetics

The extent of percutaneous absorption of topical corticosteroids is determined by many factors including the vehicle, the integrity of the epidermal barrier, and the use of occlusive dressings.

Topical corticosteroids can be absorbed from normal intact skin. Inflammation and/or other disease processes in the skin increase percutaneous absorption. Occlusive dressings substantially increase the percutaneous absorption of topical corticosteroids. Thus, occlusive dressings may be a valuable therapeutic adjunct for treatment of resistant dermatoses.

(See DOSAGE AND ADMINISTRATION).

Once absorbed through the skin, topical corticosteroids are handled through pharmacokinetic pathways similar to systemically administered corticosteroids. Corticosteroids are bound to plasma proteins in varying degrees. Corticosteroids are metabolized primarily in the liver and are then excreted by the kidneys. Some of the topical corticosteroids and their metabolites are also excreted into the bile.

INDICATIONS AND USAGE

Topical corticosteroids are indicated for the relief of the inflammatory and pruritic manifestations of corticosteroid-responsive dermatoses.

CONTRAINDICATIONS

Topical corticosteroids are contraindicated in those patients with a history of hypersensitivity to any of the components of the preparation.

PRECAUTIONS

General

Systemic absorption of topical corticosteroids has produced reversible hypothalamic-pituitary-adrenal (HPA) axis suppression, manifestations of Cushing's syndrome, hyperglycemia, and glucosuria in some patients.

Conditions which augment systemic absorption include the application of the more potent steroids, use over large surface areas, prolonged use, and the addition of occlusive dressings.

Therefore, patients receiving a large dose of a potent topical steroid applied to a large surface area or under an occlusive dressing should be evaluated periodically for evidence of HPA axis suppression by using the urinary free cortisol and ACTH stimulation tests. If HPA axis suppression is noted, an attempt should be made to withdraw the drug, to reduce the frequency of application, or to substitute a less potent steroid.

Recovery of HPA axis function is generally prompt and complete upon discontinuation of the drug. Infrequently, signs and symptoms of steroid withdrawal may occur, requiring supplemental systemic corticosteroids.

Children may absorb proportionally larger amounts of topical corticosteroids and thus be more susceptible to systemic toxicity. (See PRECAUTIONS-Pediatric Use).

If irritation develops, topical corticosteroids should be discontinued and appropriate therapy instituted.

In the presence of dermatological infections, the use of an appropriate antifungal or antibacterial agent should be instituted. If a favorable response does not occur promptly, the corticosteroid should be discontinued until the infection has been adequately controlled.

Information for the Patient

Patients using topical corticosteroids should receive the following information and instructions:

1. This medication is to be used as directed by the physician. It is for external use only. Avoid contact with the eyes.
2. Patients should be advised not to use this medication for any disorder other than for which it was prescribed.
3. The treated skin area should not be bandaged or otherwise covered or wrapped as to be occlusive unless directed by the physician.
4. Patients should report any signs of local adverse reactions especially under occlusive dressing.
5. Parents of pediatric patients should be advised not to use tight-fitting diapers or plastic pants on a child being treated in the diaper area, as these garments may constitute occlusive dressings.

Laboratory Tests

The following tests may be helpful in evaluating the HPA axis suppression:

Urinary free cortisol test
ACTH stimulation test

Carcinogenesis, Mutagenesis, and Impairment of Fertility

Long-term animal studies have not been performed to evaluate the carcinogenic potential or the effect on fertility of topical corticosteroids.

Studies to determine mutagenicity with prednisolone and hydrocortisone have revealed negative results.

Pregnancy Category C

Corticosteroids are generally teratogenic in laboratory animals when administered systemically at relatively low dosage levels. The more potent corticosteroids have been shown to be teratogenic after dermal application in laboratory animals. There are no adequate and well-controlled studies in pregnant women on teratogenic effects from topically applied corticosteroids. Therefore, topical corticosteroids should be used during pregnancy only if the potential benefit justifies the potential risk to the fetus. Drugs of this class should not be used extensively on pregnant patients, in large amounts, or for prolonged periods of time.

Nursing Mothers

It is not known whether topical administration of corticosteroids could result in sufficient systemic absorption to produce detectable quantities in breast milk. Systemically administered corticosteroids are secreted into breast milk in quantities not likely to have deleterious effect on the infant. Nevertheless, caution should be exercised when topical corticosteroids are administered to a nursing woman.

Pediatric Use

Pediatric patients may demonstrate greater susceptibility to topical corticosteroid-induced HPA axis suppression and Cushing's syndrome than mature patients because of a larger skin surface area body weight ratio.

Hypothalamic-pituitary-adrenal (HPA) axis suppression, Cushing's syndrome, and intracranial hypertension have been reported in children receiving topical corticosteroids. Manifestations of adrenal suppression in children include linear growth retardation, delayed weight gain, low plasma cortisol levels, and absence of response to ACTH stimulation. Manifestations of intracranial hypertension include bulging fontanelles, headaches, and bilateral papilledema.

Administration of topical corticosteroids to children should be limited to the least amount compatible with an effective therapeutic regimen. Chronic corticosteroid therapy may interfere with the growth and development of children.

ADVERSE REACTIONS

The following local adverse reactions are reported infrequently with topical corticosteroids, but may occur more frequently with the use of occlusive dressings. These reactions are listed in an approximate decreasing order of occurrence:

Burning
Itching
Irritation
Dryness
Folliculitis
Hypertrichosis
Acneiform eruptions
Hypopigmentation
Perioral dermatitis
Allergic contact dermatitis
Maceration of the skin
Secondary infection
Skin atrophy
Striae
Miliaria

OVERDOSAGE

Topically applied corticosteroids can be absorbed in sufficient amounts to produce systemic effects (see PRECAUTIONS).

DOSAGE AND ADMINISTRATION

Apply Cloderm (clocortolone pivalate) Cream 0.1% sparingly to the affected areas three times a day and rub in gently.

Occlusive dressings may be used for the management of psoriasis or recalcitrant conditions.

If an infection develops, the use of occlusive dressings should be discontinued and appropriate anti-microbial therapy instituted.

HOW SUPPLIED

Cloderm (clocortolone pivalate) Cream 0.1% is supplied in 75 gram pump bottles, 45 gram and 90 gram tubes.

 | 75 gram pump bottle | NDC 71403-804-75
 | 45 gram tube | NDC 71403-804-45
 | 90 gram tube | NDC 71403-804-90

STORAGE

Store Cloderm Cream between 15° and 30° C (59° and 86° F). Avoid freezing.

Cloderm® is a registered trademark of EPI Health, LLC

Manufactured for:
EPI Health, LLC
Charleston, SC 29403

EPIHEALTH
Advancing Dermatology

REV 1118
CLO-PI-1118

PRINCIPAL DISPLAY PANEL - 45 g Tube Label

Cloderm®
(clocortolone pivalate)

Rx Only
For Topical Use Only
Net Wt 45 g

NDC 71403-804-45

Cream, 0.1%

EPIHEALTH
Advancing Dermatology